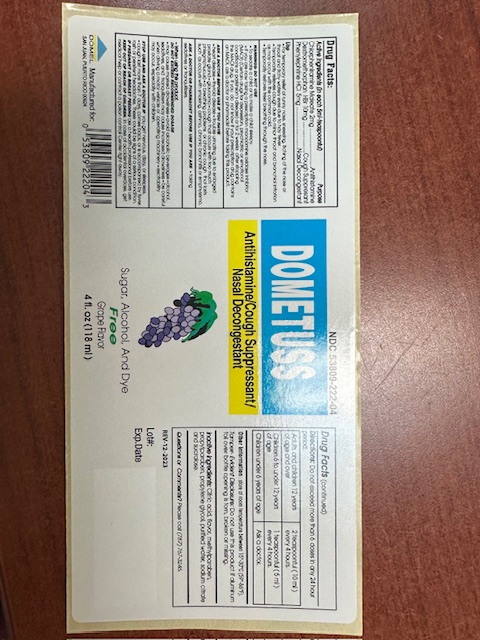 DRUG LABEL: Dometuss
NDC: 65852-002 | Form: LIQUID
Manufacturer: Dextrum Laboratories, Inc
Category: otc | Type: HUMAN OTC DRUG LABEL
Date: 20250927

ACTIVE INGREDIENTS: CHLORPHENIRAMINE MALEATE 2 mg/5 mL; PHENYLEPHRINE HYDROCHLORIDE 5 mg/5 mL; DEXTROMETHORPHAN HYDROBROMIDE 10 mg/5 mL
INACTIVE INGREDIENTS: METHYLPARABEN; CITRIC ACID MONOHYDRATE; PROPYLPARABEN; SUCRALOSE; WATER; SODIUM CITRATE MONOHYDRATE; PROPYLENE GLYCOL

Dometuss

PURPOSE

Anthistamine

cough suppresant

nasal descongestant.

Use

For temporary relief of runny nose, sneezing, itching of the nose orthroat and itchywatery eyes due to hay fever.

Temporary relieves cough due to minor throat and bronchial irritation as may occur with the common cold.

temporary restores freer breathing through the nose.

Active Ingredients (in each 5ml-teaspoonful)

Chlorpheniramine Maleate 2mg

Dextromethorphan HBr 10mg

Phenylephrine HCl 5mg

Warnings: Do not use

- To sedate a child or to make a child sleepy.
- If you are now taking a prescription monoamine oxidose inhibitor (MAOI) (Certain drugs for depression, psychiatric or emotional conditiosn or parkinson's disease) or for 2 weeks after stopping the MAOI drug. If you do not know if your prescription drug contains an MAOI, asl a doctor or pharmacist before taking this product.

Ask a Doctor Before use if you have

heart disease, thyroid disease trouble urinating due to enlarged prostate gland, glaucoma, cough that occurs with too much phlegm (mucus), a breathing problems or chronic cough that lasts such as occurs with smoking, asthma, chronic bronchitis or emphysema.

When using this product do not exceed recommended dosage

may cause marked drowsiness, avoid alcoholic beverages

alcohol, sedatives and tranquilizers may cause increased drowsiness

be carefulwhen driving a motor vehicleor operating machinery

excitability may occur, especially with children

Stop use and ask a doctor if:

You get nervous, dizzy, or sleepless.

Cough last more than 7 days, comes back, or is accompanied by fiver, rash or persistent headaches. These could be signs of a serious condition.

If pregnant

If pregnant or breast feeding ask a health professional before use.

Keep Out

Keep out of reach of children.

In case of accidental overdose, get medical help or contact a poison Control center right away.

Directions

Do not exceed more than 6 doses in a 24 hour period.

Adults and children 12 years of age and over 2 teaspoonful (10 ml) every 4 hours.

Children 6 to under 12 years of age 1 teaspoonful (5 ml) every 4 hours.

Children under 6 years of age Ask a doctor.

Other information

Other information: store at room temperature between 15-30 C(59-86 F)

Tamper-Evident

Tamper-Evident Disclosure: Do not use this product if aluminum foil over bottle opening is torn, broken or missing.

Inactive Ingredients

Citric Acid, flavor, methylparaben, propylparaben, propylene glycol, purified water, sodium citrate and sucralose.

Question

Questions or Comments? Please call (787)767-3246.

Indication and usage section

:

Indication and usage section:

adults and children 12 year of age and over--- 2 teaspoonful (10ml) every 4 hours

Childrens 6 to under 12 years of age------ i teaspoonful (5ml) every 4 hours

Childrens under 6 years of age------ask a doctor

Do not exceed more than 6 doses in any 24 hours period.

PACKAGE LABEL

Dometuss

Antihistamine/Cough Suppressant/Nasal Decongestant

Sugar, Alcohol, And Dye

Free

Grape Flavor

4 fl oz (118 ml)